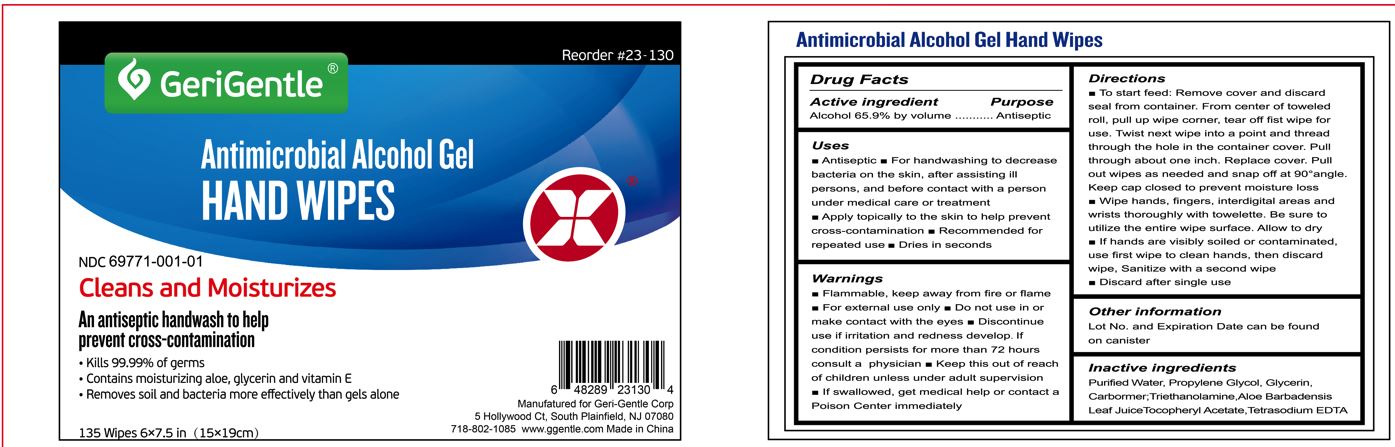 DRUG LABEL: GeriGentle Hand Wipes
NDC: 69771-001 | Form: GEL
Manufacturer: Geri-Gentle Corporation
Category: otc | Type: HUMAN OTC DRUG LABEL
Date: 20231110

ACTIVE INGREDIENTS: ALCOHOL 69.5 g/100 g
INACTIVE INGREDIENTS: PROPYLENE GLYCOL; GLYCERIN; ALOE VERA LEAF; TROLAMINE; CARBOMER 934; WATER; ALPHA-TOCOPHEROL ACETATE; EDETATE SODIUM

GeriGentle Antimicrobial Alcohol Gel Hand Wipes

Active Ingredient

Active Ingredient Purpose Alcohol 65.9% by volume Antiseptic

Purpose

Antiseptic

Uses

- Antiseptic.
- For hand washing to decrease bacteria on the skin, after assisting ill persons and before contact with a person under medical care or treatment.
- Apply topically to the skin to help prevent cross contamination.
- Recommended for repeated use.
- Dries in seconds

Warnings

- Flammable, keep away from fire or flame.
- For external use only.

Do Not Use

in or contact the eye

Stop Use

- Discontinue Use

if irritation and redness develop, If condition persists for more than 72 hours consult a physician.

Directions

- To start the feed of the wipes: Remove cover and discard seal from container, from the center of the towel roll pull up the corner of the wipe and tear off that wipe. Twist the next wipe into a point and thread through the hole in the container cover. Pull through only about one inch. Replace the cover, pull up wipes as needed and snap off at 90 angle. Keep cover closed to prevent moisture loss.^0
- Wipe hands, fingers, inter-digital areas and wrists thoroughly with towelette. Be sure to utilize the entire wipes surface. Allow to dry.
- If hands are visibly soiled or contaminated, use first wipe to clean hands, then discard wipe, sanitize with a second wipe.
- Discard after single use.

Inactive Ingredients

Inactive Ingredients: Aloe Barbadensis Leaf Juice, Carbomer, Glycerin, Propylene Glycol, Tetrasodium EDTA, Tocopheryl Acetate, Triethanolamine, Water.

Keep Out Of Reach Of Children

- Unless under adult supervision,
- If swallowed, get medical help or contact the Poison Control Center

Other Information

Lot No. and Expiration Date can be found on the canister

Principal Display Panel

4